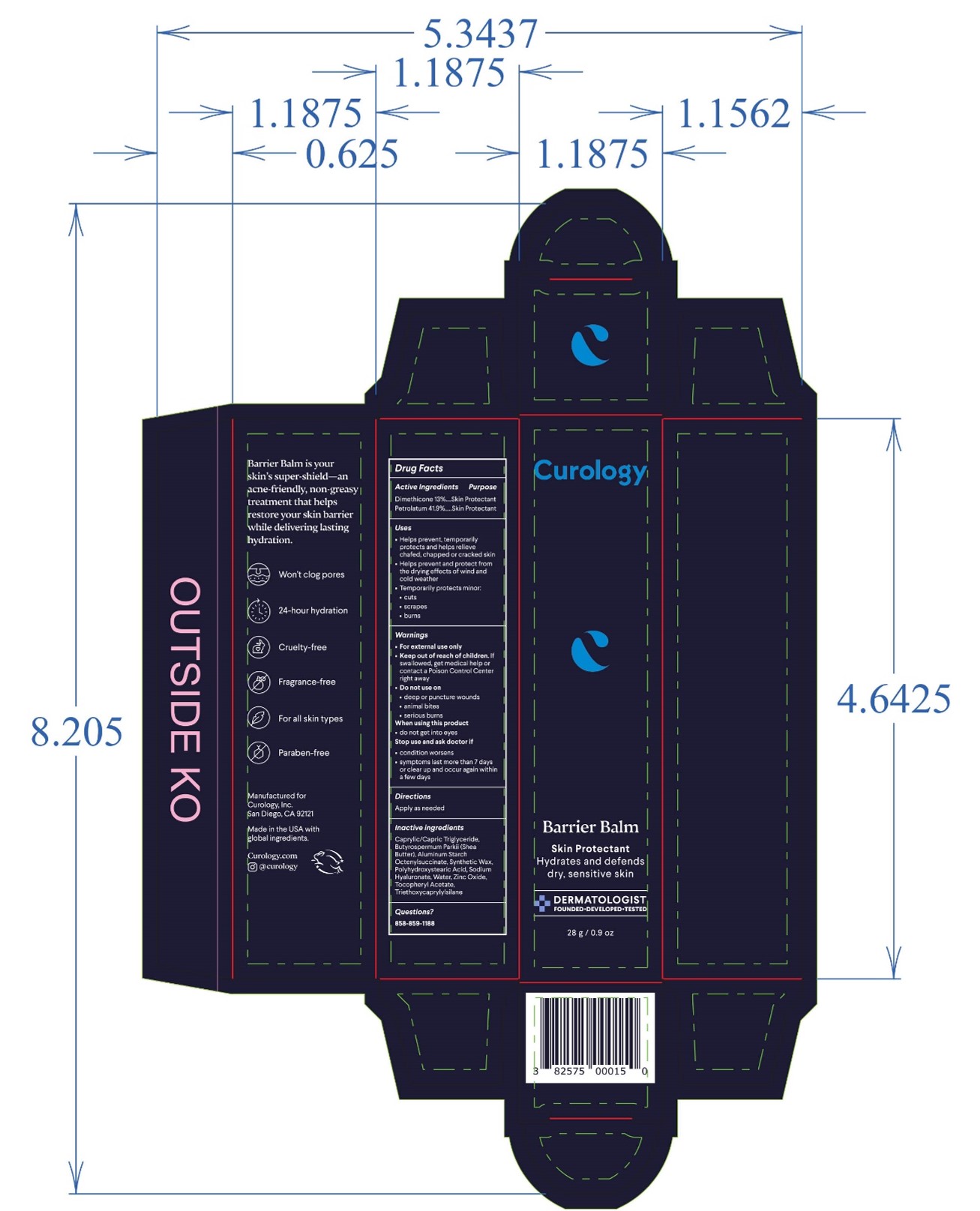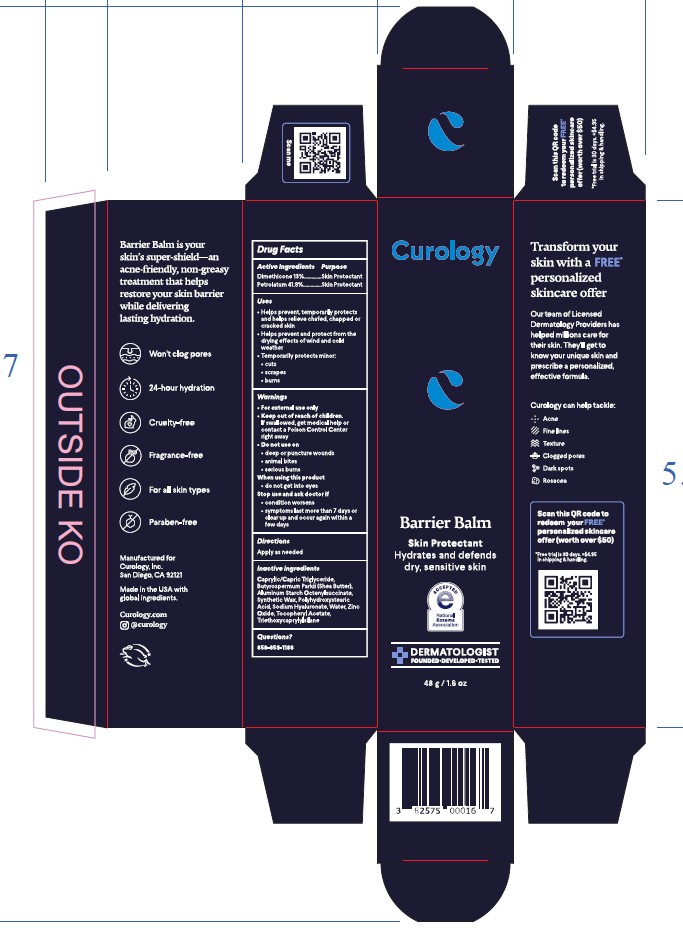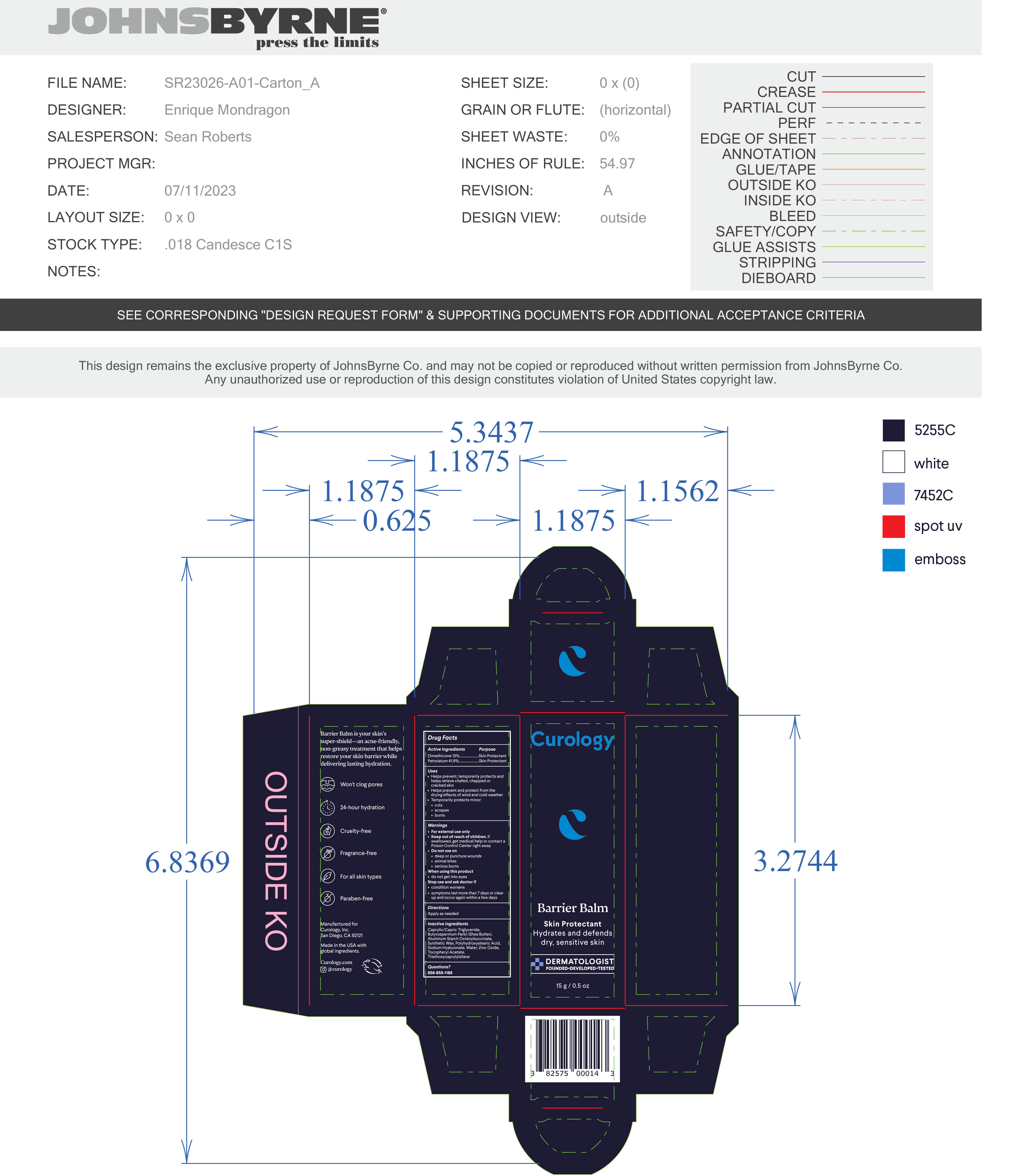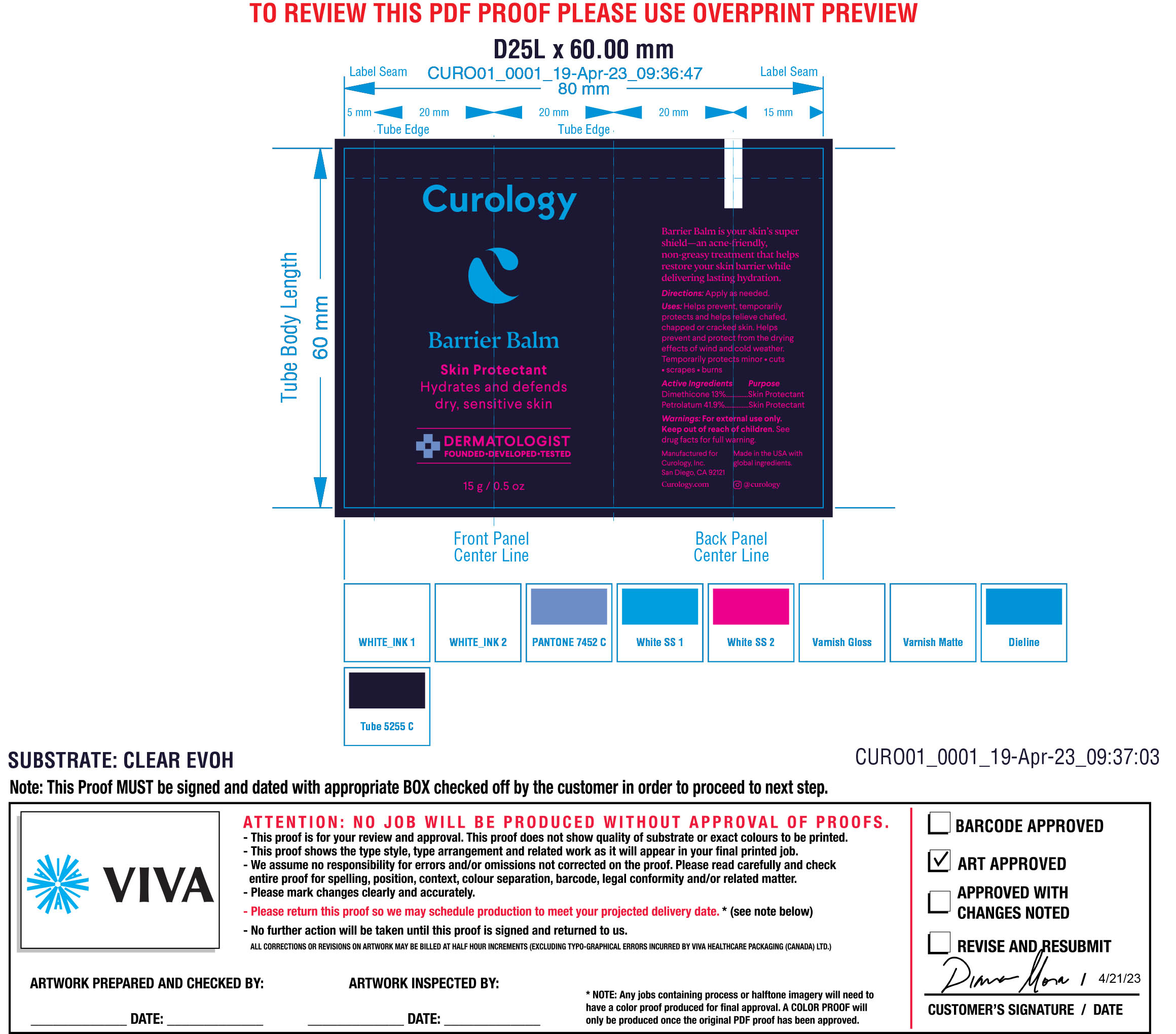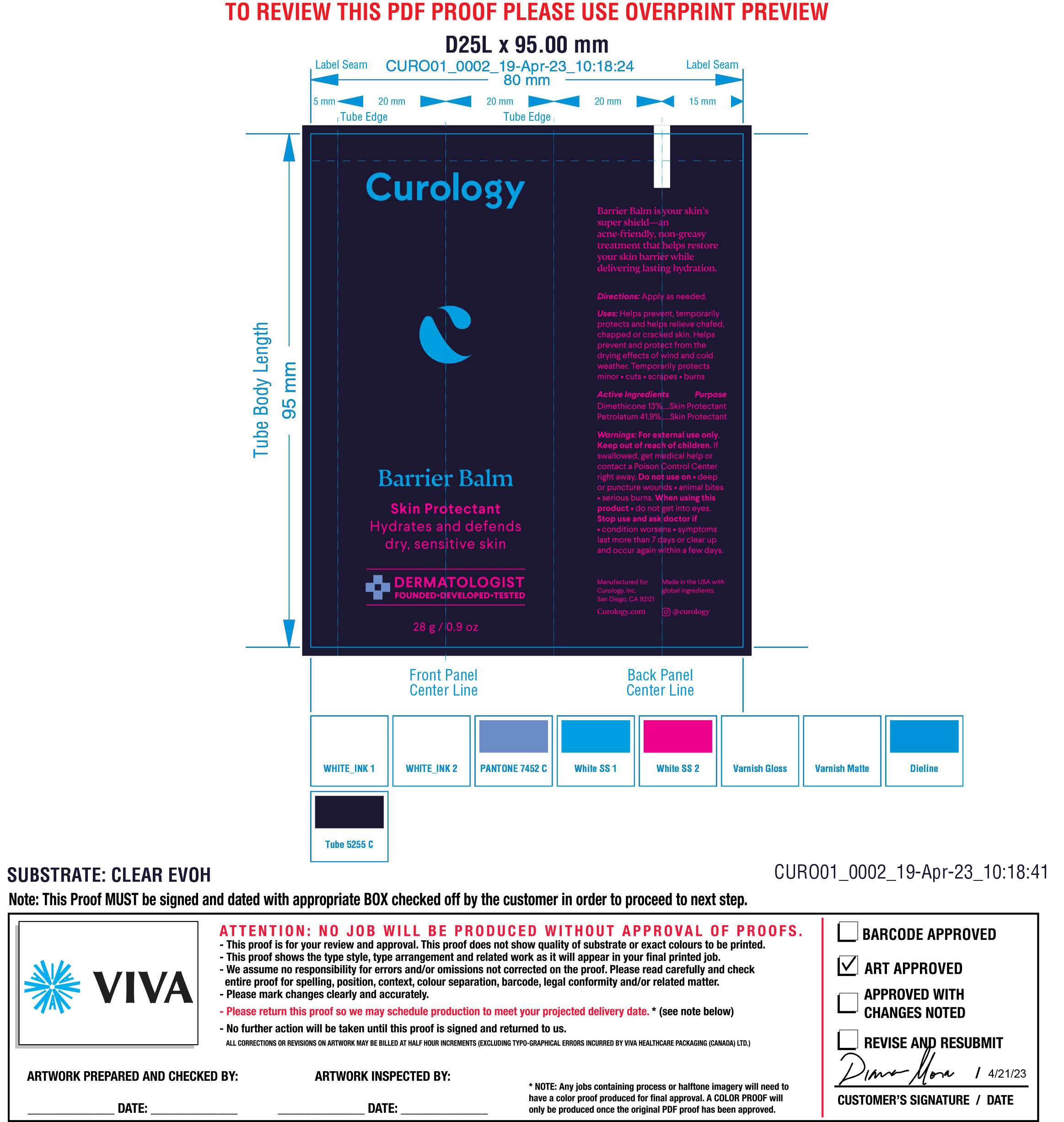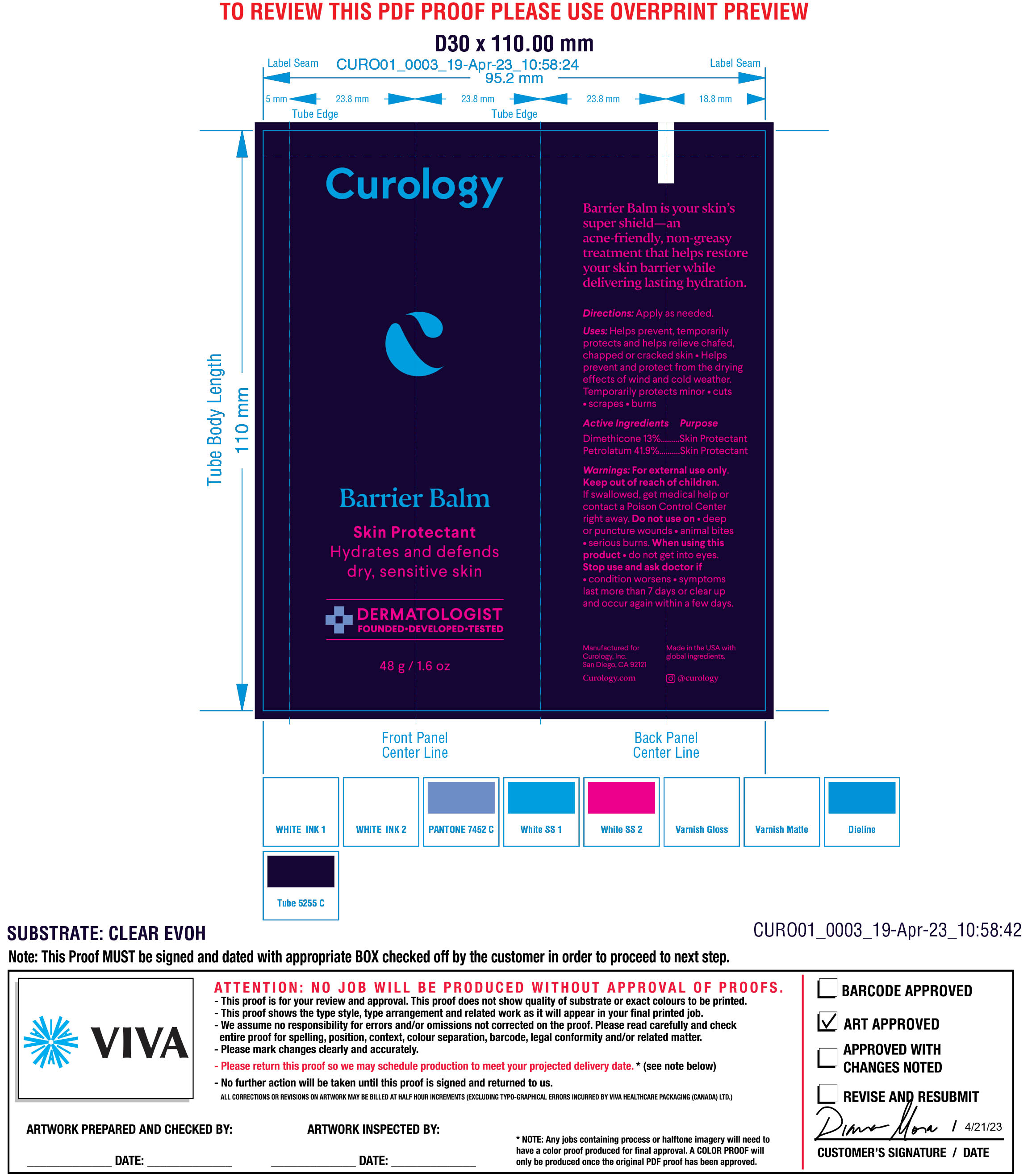 DRUG LABEL: Curology Barrier Balm
NDC: 82575-302 | Form: OINTMENT
Manufacturer: Curology
Category: otc | Type: HUMAN OTC DRUG LABEL
Date: 20251015

ACTIVE INGREDIENTS: DIMETHICONE 20 13 g/100 g; PETROLATUM 41.9 g/100 g
INACTIVE INGREDIENTS: .ALPHA.-TOCOPHEROL ACETATE, DL-; SHEA BUTTER; WATER; POLYHYDROXYSTEARIC ACID (2300 MW); TRIETHOXYCAPRYLYLSILANE; SYNTHETIC WAX (1800 MW); ZINC OXIDE; BUTYLATED HYDROXYTOLUENE; MEDIUM-CHAIN TRIGLYCERIDES; ALUMINUM STARCH OCTENYLSUCCINATE

CUROLOGY - Barrier Balm (82575-302)

ACTIVE INGREDIENT

Dimethicone 13%

Petrolatum 41.9%

PURPOSE

Skin Protectant

Uses

- Helps prevent, temporarily protects and helps relieve chafed, chapped or cracked skin
- Helps prevent and protect from the drying effects of wind and cold weather
- Temporarily protects minor
  1. cuts
  2. scrapes
  3. burns

For External Use Only

Apply as needed

WARNINGS

For external use only

Keep out of reach of children. If swallowed, get medical help or contact a Poison Control Center right away

Do not use on

- deep or puncture wounds
- animal bites
- serious burns

When using this product

- do not get into eyes

Stop use and ask doctor if

- condition worsens
- symptoms last more than 7 days or clear up and occur again within a few days

INACTIVE INGREDIENT

Caprylic/Capric Triglyceride, Butyrospermum Parkii (Shea) Butter, Aluminum Starch Octenylsuccinate, Synthetic Wax, Polyhydroxystearic Acid, Water, Zinc Oxide, Tocopheryl Acetate, Sodium Hyaluronate, Triethoxycaprylylsilane, BHT.

Questions?

858-859-1188

Keep out of reach of children. If swallowed, get medical help or contact a Poison Control Center right away

Directions

Apply as needed